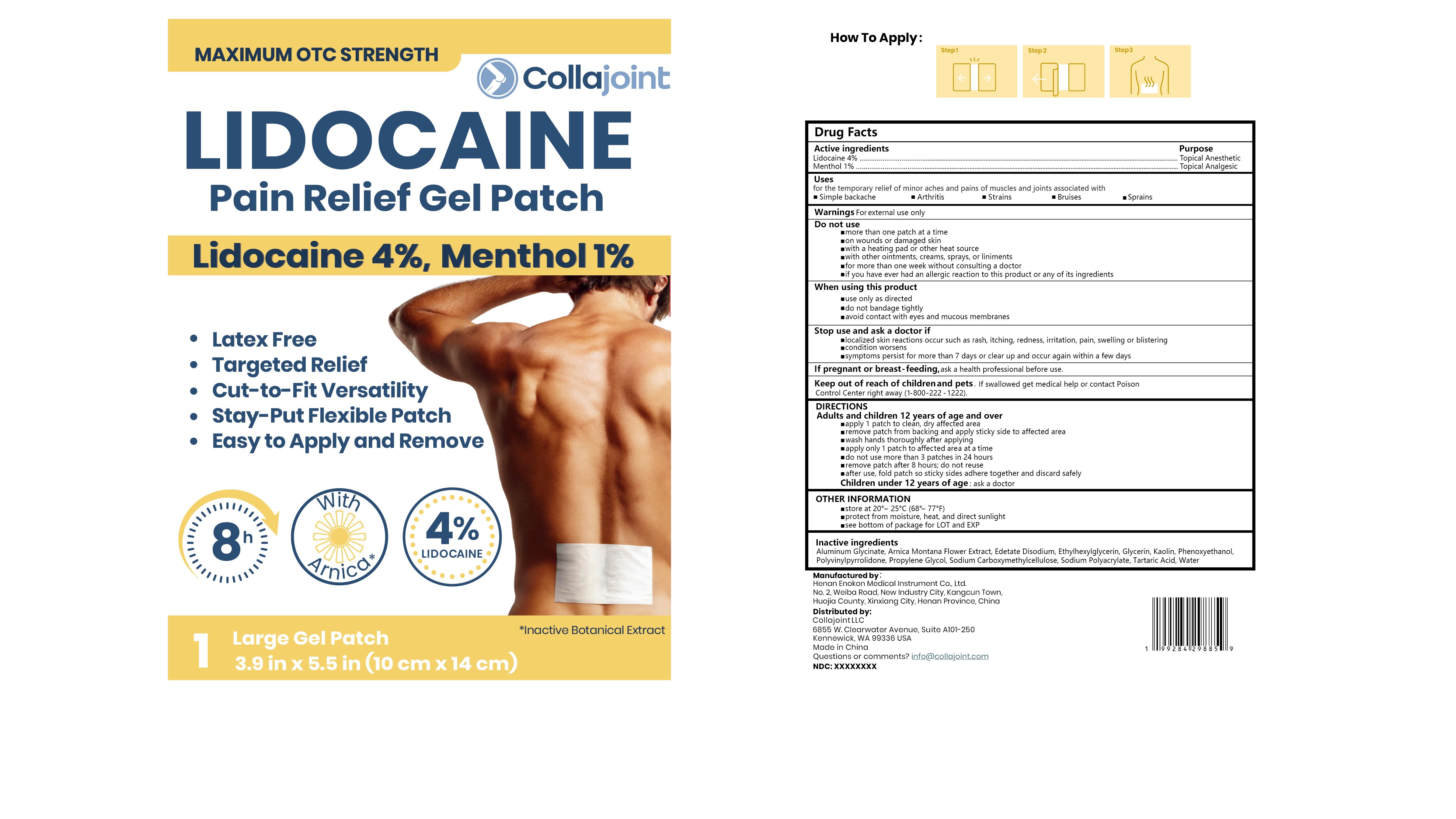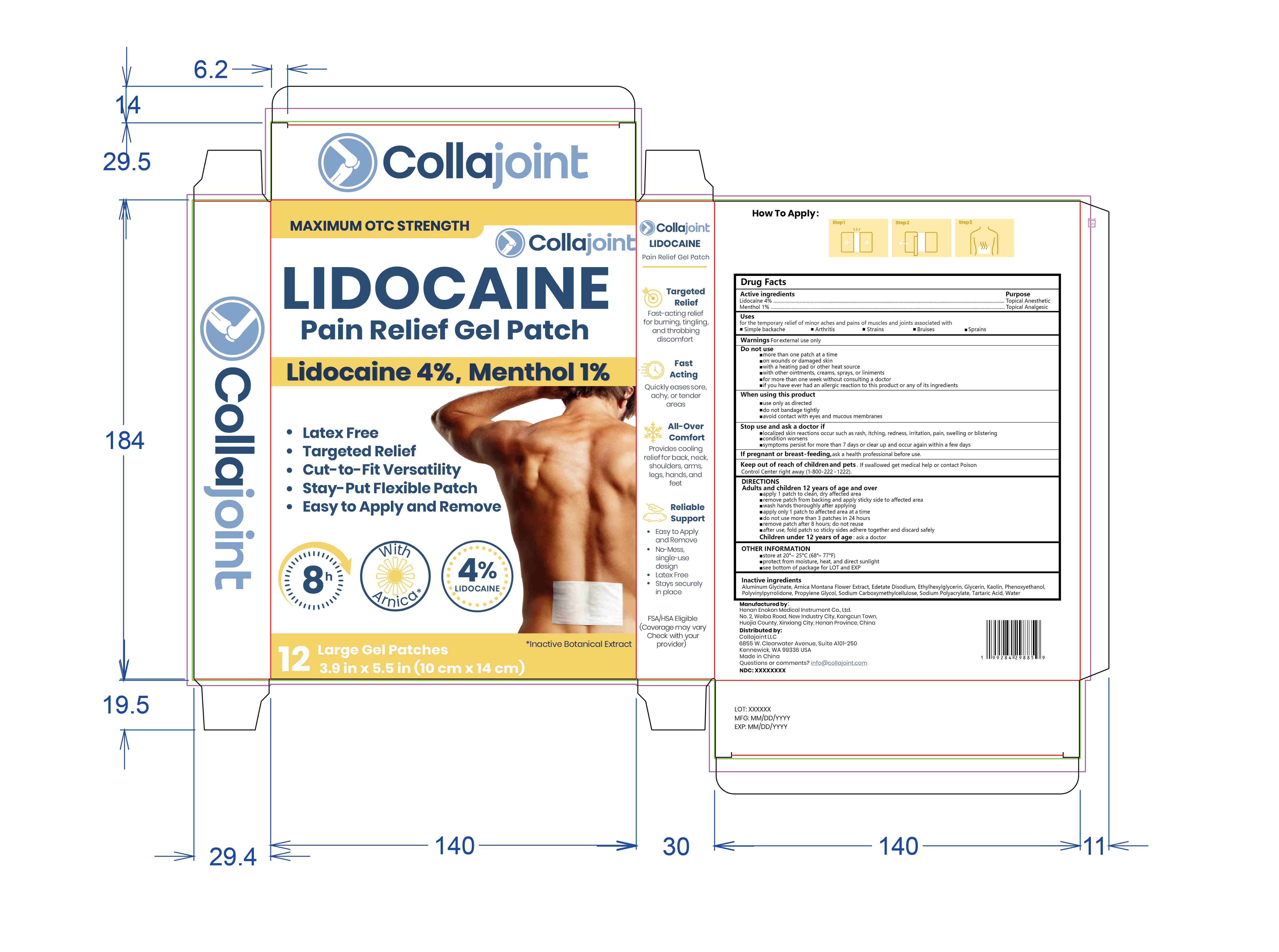 DRUG LABEL: Collajoint Lidocaine Pain Relief Gel Patch
NDC: 83559-012 | Form: PATCH
Manufacturer: Henan Enokon Medical Instrument Co., Ltd.
Category: otc | Type: HUMAN OTC DRUG LABEL
Date: 20260131

ACTIVE INGREDIENTS: MENTHOL 1 g/100 1; LIDOCAINE 4 g/100 1
INACTIVE INGREDIENTS: ETHYLHEXYLGLYCERIN; CARBOXYMETHYLCELLULOSE SODIUM; WATER; EDETATE DISODIUM; KAOLIN; ALUMINUM GLYCINATE; GLYCERIN; POVIDONE; PHENOXYETHANOL; ARNICA MONTANA FLOWER; SODIUM ACRYLATE; TARTARIC ACID; PROPYLENE GLYCOL

83559-012 Active

Active Ingredient

Lidocaine 4%
Menthol 1%

Purpose

Topical anesthetic
Topical Analgesic

Use

for the temporary relief of minor aches and pains of muscles and joints associated with *Simple backache
*Arthritis *Strains *Bruises *Sprains

Warnings

For external use only

Do not use

more than one patch at a time
on wounds or damaged skin
with a heating pad or other heat source
with other ointments, creams, sprays, or liniments
for more than one week without consulting a doctor
if you have ever had an allergic reaction to this product or any of its ingredients

When Using

use only as directed
do not bandage tightly
avoid contact with eyes and mucous membranes

Stop Use

localized skin reactions occur such as rash, itching, redness, irritation, pain, swelling or blistering
condition worsens
symptoms persist for more than 7 days or clear up and occur again within a few days

Ask Doctor

If pregnant or breast-feeding,ask a health professional before use.

Keep out of reach of children and pets . lf swallowed get medical help or contact Poison
Control Center right away(1-800-222 -1222).

Directions

Adults and children 12 years of age and over
apply 1 patch to clean, dry affected area
remove patch from backing and apply sticky side to affected area
wash hands thoroughly after applying
apply only 1 patch to affected area at a time
do not use more than 3 patches in 24 hours
remove patch after 8 hours; do not reuse
after use, fold patch so sticky sides adhere together and discard safely
Children under 12 years of age: ask a doctor

Other information

store at 20°- 25°C(68°- 77°F)
protect from moisture, heat, and direct sunlight
see bottom of package for LOT and EXP

Inactive ingredients

Aluminum Glycinate, Arnica Montana Flower Extract, Edetate Disodium, Ethylhexylglycerin, Glycerin, Kaolin, Phenoxyethanol,
Polyvinylpyrrolidone, Propylene Glycol, Sodium Carboxymethylcellulose, Sodium Polyacrylate, Tartaric Acid, Water

Questions

Questions or comments?

info@collajoint.com